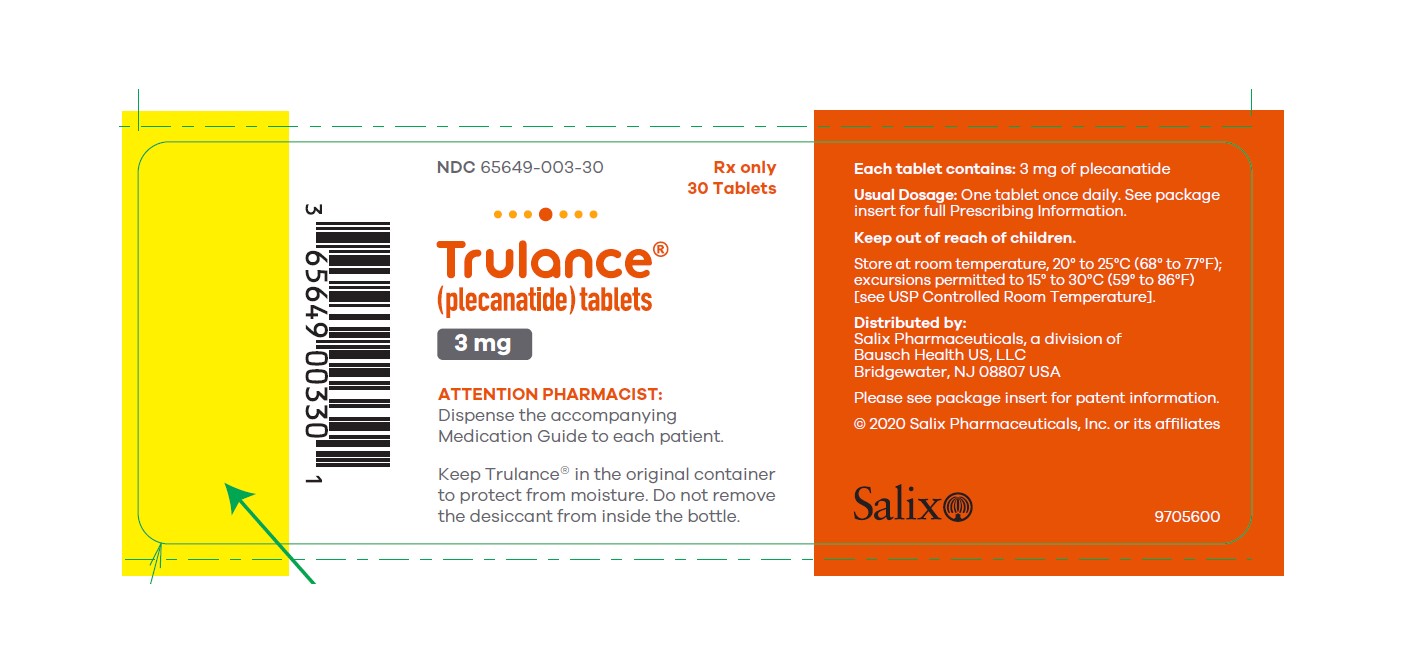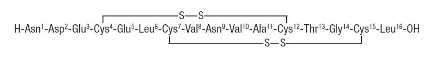 DRUG LABEL: Trulance

NDC: 65649-003 | Form: TABLET
Manufacturer: Salix Pharmaceuticals Inc.
Category: prescription | Type: HUMAN PRESCRIPTION DRUG LABEL
Date: 20240404

ACTIVE INGREDIENTS: PLECANATIDE 3 mg/1 1
INACTIVE INGREDIENTS: MAGNESIUM STEARATE; MICROCRYSTALLINE CELLULOSE

HIGHLIGHTS OF PRESCRIBING INFORMATION

These highlights do not include all the information needed to use TRULANCE safely and effectively. See full prescribing information for TRULANCE.
TRULANCE®(plecanatide) tablets, for oral use
Initial U.S. Approval: 2017

WARNING: RISK OF SERIOUS DEHYDRATION IN PEDIATRIC PATIENTS

See full prescribing information for complete boxed warning.

- TRULANCE is contraindicated in patients less than 6 years of age; in young juvenile mice, plecanatide caused death due to dehydration. (4, 8.4)
- Avoid use of TRULANCE in patients 6 years to less than 18 years of age. (5.1, 8.4)
- The safety and effectiveness of TRULANCE have not been established in patients less than 18 years of age. (8.4)

1 INDICATIONS AND USAGE

TRULANCE is a guanylate cyclase-C agonist indicated in adults for treatment of:

- chronic idiopathic constipation (CIC). (1)
- irritable bowel syndrome with constipation (IBS-C). (1)

2 DOSAGE AND ADMINISTRATION

The recommended adult dosage of TRULANCE is

- CIC: 3 mg taken orally once daily. (2.1)
- IBS-C: 3 mg taken orally once daily. (2.1)

Administration Instructions (2.2):

- Take with or without food.
- Swallow tablets whole.
- For patients who have difficulty swallowing tablets whole or those with a nasogastric or gastric feeding tube, see full prescribing information with instructions for crushing the tablet and administering with applesauce or water.

3 DOSAGE FORMS AND STRENGTHS

Tablets: 3 mg (3)

4 CONTRAINDICATIONS

- Patients less than 6 years of age due to the risk of serious dehydration. (4, 5.1, 8.4)
- Patients with known or suspected mechanical gastrointestinal obstruction. (4)

5 WARNINGS AND PRECAUTIONS

Diarrhea: Patients may experience severe diarrhea. If severe diarrhea occurs, suspend dosing and rehydrate the patient. (5.2)

6 ADVERSE REACTIONS

Most common adverse reaction (≥2%) is diarrhea. (6.1)

To report SUSPECTED ADVERSE REACTIONS, contact Salix Pharmaceuticals at 1-800-321-4576 or FDA at 1-800-FDA-1088 or www.fda.gov/medwatch.

FULL PRESCRIBING INFORMATION

WARNING: RISK OF SERIOUS DEHYDRATION IN PEDIATRIC PATIENTS

- TRULANCE is contraindicated in patients less than 6 years of age; in nonclinical studies in young juvenile mice, administration of a single oral dose of plecanatide caused deaths due to dehydration [see Contraindications (4), Use in Specific Populations (8.4)] .
- Avoid use of TRULANCE in patients 6 years to less than 18 years of age [see Warnings and Precautions (5.1), Use in Specific Populations (8.4)] .
- The safety and effectiveness of TRULANCE have not been established in patients less than 18 years of age [see Use in Specific Populations (8.4)] .

1 INDICATIONS AND USAGE

TRULANCE is indicated in adults for the treatment of:

- chronic idiopathic constipation (CIC).
- irritable bowel syndrome with constipation (IBS-C).

2 DOSAGE AND ADMINISTRATION

2.1 Recommended Dosage

The recommended dosage of TRULANCE for the treatment of CIC and IBS-C is 3 mg taken orally once daily.

2.2 Preparation and Administration Instructions

- Take TRULANCE with or without food [see Clinical Pharmacology (12.3)] .
- If a dose is missed, skip the missed dose and take the next dose at the regular time. Do not take two doses at the same time.
- Swallow a tablet whole for each dose.
- For adult patients with swallowing difficulties, TRULANCE tablets can be crushed and administered orally either in applesauce or with water or administered with water via a nasogastric or gastric feeding tube. Mixing TRULANCE crushed tablets in other soft foods or in other liquids has not been tested.

Oral Administration in Applesauce:

1. In a clean container, crush the TRULANCE tablet to a powder and mix with 1 teaspoonful of room temperature applesauce.
2. Consume the entire tablet-applesauce mixture immediately. Do not store the mixture for later use.

Oral Administration in Water:

1. Place the TRULANCE tablet in a clean cup.
2. Pour approximately 30 mL of room temperature water into the cup.
3. Mix by gently swirling the tablet and water mixture for at least 10 seconds. The TRULANCE tablet will fall apart in the water.
4. Swallow the entire contents of the tablet-water mixture immediately.
5. If any portion of the tablet is left in the cup, add another 30 mL of water to the cup, swirl for at least 10 seconds, and swallow immediately.
6. Do not store the tablet-water mixture for later use.

Administration with Water via a Nasogastric or Gastric Feeding Tube:

1. Place the TRULANCE tablet in a clean cup with 30 mL of room temperature water.
2. Mix by gently swirling the tablet and water mixture for at least 15 seconds. The TRULANCE tablet will fall apart in the water.
3. Flush the nasogastric or gastric feeding tube with 30 mL of water using a catheter tip syringe.
4. Draw up the mixture using the syringe and immediately administer via the nasogastric or gastric feeding tube. Do not reserve for future use.
5. If any portion of the tablet is left in the cup, add another 30 mL of water to the cup, swirl for at least 15 seconds, and using the same syringe, administer via the nasogastric or gastric feeding tube.
6. Using the same or a fresh syringe, flush the nasogastric or gastric feeding tube with at least 10 mL of water.

3 DOSAGE FORMS AND STRENGTHS

TRULANCE Tablets:

3 mg: white to off-white, plain, round tablet debossed with “SP” on one side and “3” for 3 mg on the other side.

4 CONTRAINDICATIONS

TRULANCE is contraindicated in:

- Patients less than 6 years of age due to the risk of serious dehydration [see Warnings and Precautions (5.1), Use in Specific Populations (8.4)] .
- Patients with known or suspected mechanical gastrointestinal obstruction.

5 WARNINGS AND PRECAUTIONS

5.1 Risk of Serious Dehydration in Pediatric Patients

TRULANCE is contraindicated in patients less than 6 years of age. The safety and effectiveness of TRULANCE in patients less than 18 years of age have not been established. In young juvenile mice (human age equivalent of approximately 1 month to less than 2 years), plecanatide increased fluid-secretion into the intestines as a consequence of stimulation of guanylate cyclase-C (GC-C), resulting in mortality in some mice within the first 24 hours, apparently due to dehydration. Due to increased intestinal expression of GC-C, patients less than 6 years of age may be more likely than patients 6 years of age and older to develop severe diarrhea and its potentially serious consequences.

Avoid the use of TRULANCE in patients 6 years to less than 18 years of age. Although there were no deaths in older juvenile mice, given the deaths in younger mice and the lack of clinical safety and efficacy data in pediatric patients, avoid the use of TRULANCE in patients 6 years to less than 18 years of age [see Contraindications (4), Warnings and Precautions (5.2), Use in Specific Populations (8.4)] .

5.2 Diarrhea

Diarrhea was the most common adverse reaction in four placebo-controlled clinical trials, two in patients with CIC and two in patients with IBS-C. Severe diarrhea was reported in 0.6% of patients in two trials in patients with CIC and in 0.6% of patients in the two trials in patients with IBS-C [see Adverse Reactions (6.1)] . If severe diarrhea occurs, suspend dosing and rehydrate the patient.

6 ADVERSE REACTIONS

6.1 Clinical Trials Experience

Because clinical studies are conducted under widely varying conditions, adverse reaction rates observed in the clinical trials of a drug cannot be directly compared with rates in the clinical trials of another drug and may not reflect the rates observed in practice.

Demographic characteristics were comparable between the TRULANCE and placebo groups in all studies [see Clinical Studies (14)] .

Chronic Idiopathic Constipation (CIC)

The safety data described below reflect data from 1,733 adult patients with CIC randomized in two double-blind, placebo-controlled clinical trials (Study 1 and Study 2) to receive placebo or 3 mg of TRULANCE once daily for 12 weeks.

Most Common Adverse Reactions

Table 1 provides the incidence of adverse reactions reported in at least 2% of CIC patients in the TRULANCE-treated group and at an incidence that was greater than in the placebo group.

Table 1: Most Common Adverse Reactionsain Two Placebo-Controlled Trials of TRULANCE [Study 1 and Study 2] in Patients with CIC
Adverse Reaction | TRULANCE, 3 mg (N = 863) % | Placebo (N = 870) %
Diarrheaᵇ | 5 | 1
a:Reported in at least 2% of TRULANCE-treated patients with CIC and at an incidence greater than placebo.
b:Verbatim reports of diarrhea were recorded as adverse reactions; reports of loose stools and increase in stool frequency were recorded as adverse reactions if they were also reported to be bothersome to the patient.

Diarrhea

The majority of reported cases of diarrhea occurred within 4 weeks of treatment initiation. Severe diarrhea was reported in 0.6% of TRULANCE-treated patients compared to 0.3% of placebo-treated patients. Severe diarrhea was reported to occur within the first 3 days of treatment [see Warnings and Precautions (5.2)] .

Adverse Reactions Leading to Discontinuation

Discontinuations due to adverse reactions occurred in 4% of TRULANCE-treated patients and 2% of placebo-treated patients. The most common adverse reaction leading to discontinuation was diarrhea: 2% of TRULANCE-treated patients and 0.5% of placebo-treated patients withdrew due to diarrhea .

Less Common Adverse Reactions

Adverse reactions reported in less than 2% of TRULANCE-treated patients and at an incidence greater than placebo were: sinusitis, upper respiratory tract infection, abdominal distension, flatulence, abdominal tenderness, and increased liver biochemical tests (2 patients with alanine aminotransferase (ALT) greater than 5 to 15 times the upper limit of normal and 3 patients with aspartate aminotransferase (AST) greater than 5 times the upper limit of normal).

Irritable Bowel Syndrome with Constipation (IBS-C)

The safety data described below reflect data from 1,449 adults patients with IBS-C randomized in two double-blind, placebo-controlled clinical trials (Study 3 and Study 4) to receive placebo or 3 mg TRULANCE once daily for 12 weeks.

Most Common Adverse Reactions

Table 2 provides the incidence of adverse reactions reported in at least 2% of IBS-C patients treated with TRULANCE and at an incidence that was greater than in the placebo group.

Table 2: Most Common Adverse Reactionsain Two Placebo-Controlled Trials of TRULANCE [Study 3 and Study 4] in Patients with IBS-C
Adverse Reaction | TRULANCE, 3 mg (N = 723) % | Placebo (N = 726) %
Diarrheab | 4.3 | 1
a:Reported in at least 2% of TRULANCE-treated patients with IBS-C and at an incidence greater than placebo.
b:Verbatim reports of diarrhea were recorded as adverse reactions; reports of loose stools and increase in stool frequency were recorded as adverse reactions if they were also reported to be bothersome to the patient.

Diarrhea

The majority of reported cases of diarrhea occurred within 4 weeks of treatment initiation. Severe diarrhea was reported in 1% of TRULANCE-treated patients compared to 0.1% of placebo-treated patients [see Warnings and Precautions (5.2)] . Severe diarrhea was reported to occur within the first day of treatment.

Adverse Reactions Leading to Discontinuation

Discontinuations due to adverse reactions occurred in 2.5% of TRULANCE-treated patients and 0.4% of placebo-treated patients. The most common adverse reaction leading to discontinuation was diarrhea: 1.2% of TRULANCE-treated patients and 0% of placebo-treated patients withdrew due to diarrhea .

Less Common Adverse Reactions

Adverse reactions reported in 1% or more but less than 2% of TRULANCE-treated patients and at an incidence greater than placebo were: nausea, nasopharyngitis, upper respiratory tract infection, urinary tract infection, and dizziness. Two patients reported increased liver biochemical tests (alanine aminotransferase (ALT) greater than 5 to 15 times the upper limit of normal).

6.2 Postmarketing Experience

The following adverse reactions have been identified during post-approval use of TRULANCE. Because these reactions are reported voluntarily from a population of uncertain size, it is not always possible to reliably estimate their frequency or establish a causal relationship to TRULANCE exposure.

- Hypersensitivity Reactions: skin itching, hives, rash
- Vomiting

8 USE IN SPECIFIC POPULATIONS

8.1 Pregnancy

Risk Summary

Plecanatide and its active metabolite are negligibly absorbed systemically following oral administration [see Clinical Pharmacology (12.3)] and maternal use is not expected to result in fetal exposure to the drug. The available data on TRULANCE use in pregnant women are not sufficient to inform any drug-associated risks for major birth defects and miscarriage. In animal developmental studies, no effects on embryo-fetal development were observed with oral administration of plecanatide in mice and rabbits during organogenesis at doses much higher than the recommended human dosage.

The estimated background risk of major birth defects and miscarriage for the indicated population is unknown. All pregnancies have a background risk of birth defect, loss, or other adverse outcomes. In the United States general population, the estimated background risk of major birth defects and miscarriage in clinically recognized pregnancies is 2% to 4% and 15% to 20%, respectively.

Data

Animal Data

Pregnant mice and rabbits were administered plecanatide during the period of organogenesis. There was no evidence of harm to embryo-fetal development at oral doses up to 800 mg/kg/day in mice and 250 mg/kg/day in rabbits. Oral administration of up to 600 mg/kg/day in mice during organogenesis through lactation produced no developmental abnormalities or effects on growth, learning and memory, or fertility in the offspring through maturation.

- The maximum recommended human dose is approximately 0.05 mg/kg/day, based on a 60-kg body weight. Limited systemic exposure to plecanatide was achieved in animals during organogenesis (area under the plasma concentration-time curve (AUCt) = 449 ng●h/mL in rabbits given 250 mg/kg/day). Plecanatide and its active metabolite are not measurable in human plasma following administration of the recommended clinical dosage. Therefore, animal and human doses should not be compared directly for evaluating relative exposure.

8.2 Lactation

Risk Summary

After administration of multiple doses of TRULANCE 3 mg once daily for 2 weeks to nursing mothers, plecanatide and its active metabolite were not measurable in breast milk collected at 2 hours, 6 hours, and 12 hours post-dosing. In adults, concentrations of plecanatide and its active metabolite were mostly unmeasurable in plasma following multiple doses of TRULANCE 3 mg once daily for up to 12 weeks [see Clinical Pharmacology (12.3)] .

Maternal use of TRULANCE is not expected to result in clinically relevant exposure to plecanatide or its active metabolite in breastfed infants. The developmental and health benefits of breastfeeding should be considered along with the mother’s clinical need for TRULANCE and any potential adverse effects on the breastfed infant from TRULANCE or from the underlying maternal condition.

8.4 Pediatric Use

TRULANCE is contraindicated in pediatric patients less than 6 years of age. Avoid use of TRULANCE in patients 6 years to less than 18 years of age [see Contraindications (4), Warnings and Precautions (5.1)]. The safety and effectiveness of TRULANCE in patients less than 18 years of age have not been established.

In nonclinical studies, deaths occurred within 24 hours in young juvenile mice (human age equivalent of approximately 1 month to less than 2 years) following oral administration of plecanatide, as described below in Juvenile Animal Toxicity Data. Because of increased intestinal expression of GC-C, patients less than 6 years of age may be more likely than patients 6 years of age and older to develop diarrhea and its potentially serious consequences. TRULANCE is contraindicated in patients less than 6 years of age. Given the deaths in young juvenile mice and the lack of clinical safety and efficacy data in pediatric patients, avoid the use of TRULANCE in patients 6 years to less than 18 years of age.

Juvenile Animal Toxicity Data

Single oral doses of plecanatide at 0.5 mg/kg and 10 mg/kg caused mortality in young juvenile mice on postnatal days 7 and 14, respectively (human age equivalent of approximately 1 month to less than 2 years). Treatment-related increases in the weight of intestinal contents were observed in juvenile mice following single doses of plecanatide on postnatal day 14 (human age equivalent of approximately less than 2 years), consistent with increased fluid in the intestinal lumen. Although the recommended human dose is approximately 0.05 mg/kg/day, based on a 60-kg body weight, plecanatide and its active metabolite are not measurable in adult human plasma, whereas systemic absorption was demonstrated in the juvenile animal toxicity studies. Animal and human doses should not be compared directly for evaluating relative exposure.

8.5 Geriatric Use

Chronic Idiopathic Constipation (CIC)

Of 2,601 subjects in placebo-controlled clinical trials of TRULANCE, 273 (10%) were 65 years of age and over, and 47 (2%) were 75 years and over. Clinical studies of TRULANCE did not include sufficient numbers of patients aged 65 and over to determine whether they respond differently from patients 18 years to less than 65 years of age.

Irritable Bowel Syndrome with Constipation (IBS-C)

Of 1,621 subjects in the placebo-controlled clinical studies of TRULANCE, 134 (8.3%) were 65 years of age and over, and 25 (1.5%) were 75 years and over. Clinical studies of TRULANCE did not include sufficient numbers of patients aged 65 and over to determine whether they respond differently from patients 18 years to less than 65 years of age.

11 DESCRIPTION

TRULANCE (plecanatide) is a guanylate cyclase-C (GC-C) agonist. Plecanatide is a 16 amino acid peptide with the following chemical name: L-Leucine, L-asparaginyl-L-α-aspartyl-L-α-glutamyl-L-cysteinyl-L-α-glutamyl-L-leucyl-L-cysteinyl-L-valyl-L-asparaginyl-L-valyl-L-alanyl-L-cysteinyl-L-threonylglycyl-L-cysteinyl-, cyclic (4→12),(7→15)-bis(disulfide).

The molecular formula of plecanatide is C65H104N18O26S4and the molecular weight is 1682 Daltons. The amino acid sequence for plecanatide is shown below:

The solid lines linking cysteines illustrate disulfide bridges.

Plecanatide is an amorphous, white to off-white powder. It is soluble in water. TRULANCE tablets are supplied as 3 mg tablets for oral administration. The inactive ingredients are magnesium stearate and microcrystalline cellulose.

12 CLINICAL PHARMACOLOGY

12.1 Mechanism of Action

Plecanatide is a structural analog of human uroguanylin, and similarly to uroguanylin, plecanatide functions as a guanylate cyclase-C (GC-C) agonist. Both plecanatide and its active metabolite bind to GC-C and act locally on the luminal surface of the intestinal epithelium. Activation of GC-C results in an increase in both intracellular and extracellular concentrations of cyclic guanosine monophosphate (cGMP). Elevation of extracellular cGMP has been associated with a decrease in the activity of pain-sensing nerves in animal models of visceral pain. Elevation of intracellular cGMP stimulates secretion of chloride and bicarbonate into the intestinal lumen, mainly through activation of the cystic fibrosis transmembrane conductance regulator (CFTR) ion channel, resulting in increased intestinal fluid and accelerated transit. In animal models, plecanatide has been shown to increase fluid secretion into the gastrointestinal (GI) tract, accelerate intestinal transit, and cause changes in stool consistency.

In an animal model of visceral pain, plecanatide reduced abdominal muscle contractions, a measure of intestinal pain.

12.2 Pharmacodynamics

Food Effect

Subjects who received either a low-fat, low calorie (LF-LC) meal or a high fat, high calorie (HF-HC) meal reported looser stools than fasted subjects up to 24 hours after a single dose of TRULANCE 9 mg (3 times the recommended dose). In clinical studies, TRULANCE was administered with or without food [see Dosage and Administration (2.2)] .

12.3 Pharmacokinetics

Absorption

Plecanatide was minimally absorbed with negligible systemic availability following oral administration. Concentrations of plecanatide and its active metabolite in plasma were below the limit of quantitation in the majority of analyzed plasma samples after an oral TRULANCE dose of 3 mg. Therefore, standard pharmacokinetic parameters such as AUC, maximum concentration (Cmax), and half-life (t½) could not be calculated.

Food Effect

In a crossover study, 24 healthy subjects were given a single dose of TRULANCE 9 mg (3 times the recommended dose) in 3 different states: fasted; following a low-fat, low-calorie meal (LF-LC; approximately 350 calories: 17% from fat, 66% from carbohydrate, and 17% from protein); and following a high-fat, high-calorie meal (HF-HC; approximately 1,000 calories: 60% from fat, 25% from carbohydrate, and 15% from protein). Plecanatide was detected in 1 subject (fasted state) at 0.5 and 1 hour post dose. Plecanatide concentrations were below the limit of quantitation for all other time points and for all other subjects. The active metabolite was not detected in any subject.

Distribution

Given that plecanatide concentrations following clinically relevant oral doses were not measurable, plecanatide is expected to be minimally distributed in tissues. Oral plecanatide was localized to the GI tract where it exerted its effects as a GC-C agonist with negligible systemic exposure. Plecanatide exhibited little to no binding to human serum albumin or human α-1-acid glycoprotein.

Elimination

Metabolism

Plecanatide was metabolized in the GI tract to an active metabolite by loss of the terminal leucine moiety. Both plecanatide and the metabolite were proteolytically degraded within the intestinal lumen to smaller peptides and naturally occurring amino acids.

Excretion

No excretion studies have been conducted in humans. Plecanatide and its active metabolite were not measurable in plasma following administration of the recommended clinical doses.

Drug Interaction Studies

Neither plecanatide nor its active metabolite inhibited the cytochrome P450 (CYP) enzymes 2C9 and 3A4, and they did not induce CYP3A4 in vitro.

Plecanatide and its active metabolite were neither substrates nor inhibitors of the transporters P-glycoprotein (P-gp) or breast cancer resistance protein (BCRP) in vitro .

13 NONCLINICAL TOXICOLOGY

13.1 Carcinogenesis, Mutagenesis, Impairment of Fertility

Carcinogenesis

The carcinogenic potential of plecanatide was assessed in 2-year carcinogenicity studies in mice and rats. Plecanatide was not tumorigenic in mice at oral doses up to 90 mg/kg/day or in rats at oral doses up to 100 mg/kg/day. Limited systemic exposure to plecanatide was achieved at the tested dose levels in animals, whereas no detectable exposure occurred in humans. Therefore, animal and human doses should not be compared directly for evaluating relative exposure.

Mutagenesis

Plecanatide was not genotoxic in the in vitro bacterial reverse mutation (Ames) assay, in vitro mouse lymphoma mutation assay, or the in vivo mouse bone marrow micronucleus assay.

Impairment of Fertility

Plecanatide had no effect on fertility or reproductive function in male or female mice at oral doses of up to 600 mg/kg/day.

14 CLINICAL STUDIES

14.1 Chronic Idiopathic Constipation (CIC)

The efficacy of TRULANCE for the management of symptoms of CIC was established in two 12-week, double-blind, placebo-controlled, randomized, multicenter clinical studies in adult patients (Study 1 and Study 2). In the Intention-to-Treat (ITT) population, a total of 905 patients (Study 1) and 870 patients (Study 2) were randomized 1:1 to either placebo or TRULANCE 3 mg, once daily. In clinical studies, study medication was administered without respect to food intake. Demographics for these studies included an overall mean age of 45 years (range 18 to 80 years), 80% female, 72% white, and 24% black.

To be eligible for the studies, patients were required to meet modified Rome III criteria for at least 3 months prior to the screening visit, with symptom onset for at least 6 months prior to diagnosis. Rome III criteria were modified to require that patients report less than 3 defecations per week, rarely have a loose stool without the use of laxatives, not use manual maneuvers to facilitate defecations, and not meet criteria for IBS-C. In addition, patients were required to report at least two of the following symptoms:

- Straining during at least 25% of defections
- Lumpy or hard stool in at least 25% of defecations
- Sensation of incomplete evacuations for at least 25% of defecations
- Sensation of anorectal obstruction/blockage for at least 25% of defecations

Patients who met these criteria were also required to demonstrate the following during the last 2 weeks of the screening period:

- Less than 3 complete spontaneous bowel movements (CSBMs) (a CSBM is an SBM that is associated with a sense of complete evacuation) in each of the two weeks
- Bristol Stool Form Scale (BSFS) of 6 or 7 in less than 25% of spontaneous bowel movements (SBMs) (an SBM is a bowel movement occurring in the absence of laxative use)
- One out of the following three:
  - BSFS of 1 or 2 in at least 25% of defecations
  - A straining value recorded on at least 25% of days when a BM was reported
  - At least 25% of BMs result in a sense of incomplete evacuation

The efficacy of TRULANCE was assessed using a responder analysis and change-from-baseline in CSBM and SBM endpoints. Efficacy was assessed using information provided by patients on a daily basis in an electronic diary.

A responder was defined as a patient who had at least 3 CSBMs in a given week and an increase of at least 1 CSBM from baseline in the same week for at least 9 weeks out of the 12-week treatment period and at least 3 of the last 4 weeks of the study. The responder rates are shown in Table 3.

Table 3: Efficacy Responder Rates in the Two Placebo-Controlled Studies of CIC: At Least 9 of 12 Weeks and At Least 3 of the Last 4 Weeks (ITT Population)
Study 1
 | TRULANCE 3 mg (N = 453) | Placebo (N = 452) | Treatment Differencea [95% CIb]
Responderc | 21% | 10% | 11% [6.1%, 15.4%]
Study 2
 | TRULANCE 3 mg (N = 430) | Placebo (N = 440) | Treatment Differencea [95% CIb]
Responderc | 21% | 13% | 8% [2.6%, 12.4%]
a:p-value <0.005
b:CI = confidence interval
c:Primary endpoint defined as a patient who had a least 3 CSBMs in a given week and an increase of at least 1 CSBM from baseline in the same week for at least 9 weeks out of the 12-week treatment period and at least 3 of the last 4 weeks of the study.

In both studies, improvements in the frequency of CSBMs/week were seen as early as week 1 with improvement maintained through week 12. The difference between the TRULANCE group and the placebo group in the mean change of CSBMs/week frequency from baseline to week 12 was approximately 1.1 CSBMs/week.

Over the 12-week treatment period, improvements were observed in stool frequency (number of CSBMs/week and SBMs/week) and/or stool consistency (as measured by the BSFS), and/or in the amount of straining with bowel movements (amount of time pushing or physical effort to pass stool) in the TRULANCE group as compared to placebo.

Following completion of the study drug treatment period, patients continued to record data in the daily diary for a 2-week Post-Treatment Period. During this time, TRULANCE-treated patients generally returned to baseline for these study endpoints.

In Studies 1 and 2, a third randomized treatment arm of TRULANCE 6 mg once daily did not demonstrate additional treatment benefit and had a greater incidence of adverse reactions than TRULANCE 3 mg once daily. Therefore, TRULANCE 6 mg once daily is not recommended [see Dosage and Administration (2.1)].

14.2 Irritable Bowel Syndrome with Constipation (IBS-C)

The efficacy of TRULANCE for the management of symptoms of IBS-C was established in two 12-week, double-blind, placebo-controlled, randomized, multicenter clinical studies in adult patients (Study 3 and Study 4). In the Intention-to-Treat (ITT) population, a total of 699 patients (Study 3) and 754 patients (Study 4) received treatment with placebo or TRULANCE 3 mg once daily. In clinical studies, study medication was administered without respect to food intake. Demographics for these studies included an overall mean age of 44 years (range 18 to 83 years), 74% female, 73% white, and 22% black.

To be eligible, patients were required to meet the Rome III criteria for IBS for at least 3 months prior to the screening visit, with symptom onset for at least 6 months prior to diagnosis. Diagnosis required recurrent abdominal pain or discomfort at least 3 days/month in the last 3 months associated with 2 or more of 1) improvement with defecation, 2) onset associated with a change in frequency of stool, and 3) onset associated with a change in form (appearance) of stool. Patients also met the IBS-C differentiation criteria for constipation, characterized by a stool pattern such that at least 25% of defecations are hard or lumpy stools and no more than 25% of defecations are loose or watery stool.

Patients who met these criteria were excluded if they demonstrated the following during the last 2 weeks of the screening period:

- Worst abdominal pain intensity (WAPI) score of 0 on an 11-point scale for more than 2 days during each week
- An average WAPI of less than 3 for either week
- More than 3 complete spontaneous bowel movements (CSBMs) or more than six spontaneous bowel movements (SBMs) per week in either week
- Bristol Stool Form Scale (BSFS) of 7 for any SBM recorded
- More than 1 day in either week with a BSFS of 6 for any SBM recorded
- No use of rescue laxative (bisacodyl) within 72 hours before randomization

The efficacy of TRULANCE was assessed using a responder analysis based on abdominal pain intensity and a stool frequency responder (CSBM) endpoint. Efficacy was assessed using information provided by patients on a daily basis through an electronic phone diary system.

A responder was defined as a patient who met both the abdominal pain intensity and stool frequency responder criteria in the same week for at least 6 of the 12 treatment weeks. The abdominal pain intensity and stool frequency responder criteria assessed each week were defined as:

- Abdominal pain intensity responder: a patient who experienced a decrease in the weekly average of worst abdominal pain in the past 24 hours score (measured daily) of at least 30% compared with baseline weekly average.
- Stool frequency responder: a patient who experienced an increase of at least 1 CSBM per week from baseline.

The responder rates are shown in Table 4.

Table 4: Efficacy Responder Rates in the Two Placebo-Controlled Studies of IBS-C: Overall Responder for At Least 6 of the 12 Treatment Weeks (ITT Population)
Study 3
 | Placebo (N = 350) | TRULANCE 3 mg (N = 349) | Treatment Difference [95% CIa]
Responderb | 18% | 30% | 12% [6%, 18%]
Components of Responder Endpoint
Abdominal Pain Responderc | 32% | 41%
CSBM Responderd | 35% | 48%
Study 4
 | Placebo (N = 379) | TRULANCE 3 mg (N = 375) | Treatment Difference [95% CIa]
Responderb | 14% | 21% | 7% [2%, 13%]
Components of Responder Endpoint
Abdominal Pain Responderc | 23% | 33%
CSBM Responderd | 28% | 34%
a:CI = confidence interval
b:A responder for these trials was defined as a patient who met both the abdominal pain and CSBM weekly responder criteria for at least 6 of the 12 weeks.
c:An abdominal pain responder was defined as a patient who met the criteria of at least 30% reduction from baseline in weekly average of the worst daily abdominal pain, for at least 6 of the 12 weeks.
d:A CSBM responder was defined as a patient who achieved an increase in at least 1 CSBM per week, from baseline, for at least 6 of 12 weeks.

In both studies, the proportion of responders who were also weekly responders for at least 2 of the 4 treatment weeks in month 3, the last month of treatment was greater in the TRULANCE groups compared to placebo.

Over the 12-week treatment period, improvements were observed in both stool consistency (as measured by the BSFS) and in the amount of straining with bowel movements (amount of time pushing or physical effort to pass stool) in the 3 mg TRULANCE group as compared to placebo.

Following completion of the study drug treatment period, patients continued to record data in the daily diary for a 2-week Post-Treatment Period. During this time, TRULANCE-treated patients generally returned to baseline for these study endpoints.

In Studies 3 and 4, a third randomized treatment arm of TRULANCE 6 mg once daily did not demonstrate additional treatment benefit over the 3 mg dose. Therefore, TRULANCE 6 mg once daily is not recommended [see Dosage and Administration (2.1)].

16 HOW SUPPLIED/STORAGE AND HANDLING

TRULANCE tablets are packaged in a white, opaque, high-density polyethylene round bottle with a screw-top polypropylene child-resistant cap and heat-activated induction seal. Each bottle container-closure system also contains a desiccant and a polyester coil.

TRULANCE 3 mg tablets are white to off-white, plain and round, debossed with “SP” on one side and “3” for 3 mg on the other side and supplied as:

NDC Number | Size
65649-003-30 | Bottle of 30

STORAGE AND HANDLING

Store at room temperature, 20 to 25°C (68 to 77°F); excursions permitted to 15 to 30°C (59 to 86°F) [see USP Controlled Room Temperature].

Keep TRULANCE in a dry place. Protect from moisture. Keep TRULANCE in the original bottle. Do not remove desiccant from the bottle. Do not subdivide or repackage.

17 PATIENT COUNSELING INFORMATION

Advise the patient to read the FDA-approved patient labeling (Medication Guide).

Advise patients:

Diarrhea

To stop TRULANCE and contact their healthcare provider if they experience severe diarrhea [see Warnings and Precautions (5.2)] .

Accidental Ingestion

Accidental ingestion of TRULANCE in children, especially in children less than 6 years of age, may result in severe diarrhea and dehydration. Instruct patients to take steps to store TRULANCE securely and out of reach of children and to dispose of unused TRULANCE [see Contraindications (4), Warnings and Precautions (5.2)] .

Administration and Handling Instructions

- To take TRULANCE once daily with or without food [see Dosage and Administration (2.2)] .
- If a dose is missed, skip the missed dose and take the next dose at the regular time. Do not take two doses at the same time.
- To swallow TRULANCE tablets whole.
- If adult patients have swallowing difficulties, TRULANCE tablets can be crushed and administered orally in either applesauce or with water, or administered with water via a nasogastric or gastric feeding tube, as described in the Medication Guide.
- To keep TRULANCE in a dry place. Protect from moisture. Keep TRULANCE in the original bottle. Do not remove desiccant from the bottle. Do not subdivide or repackage. Remove and discard polyester coil after opening. Keep bottles closed tightly [see How Supplied/Storage and Handling (16)] .

Distributed by:
Salix Pharmaceuticals, a division of
Bausch Health US, LLC
Bridgewater, NJ 08807 USA

Patented. See https://patents.salix.com for US patent information.

TRULANCE is a trademark of Salix Pharmaceuticals, Inc. or its affiliates.

© 2024 Salix Pharmaceuticals, Inc. or its affiliates

9705704

Medication Guide
TRULANCE®(TROO lans)
(plecanatide) tablets, for oral use

What is the most important information I should know about TRULANCE?

- Do not give TRULANCE to children who are less than 6 years of age. It may harm them.
- You should not give TRULANCE to children 6 years to less than 18 years of age. It may harm them.
- See “What are the possible side effects of TRULANCE?”for more information about side effects.

What is TRULANCE?
TRULANCE is a prescription medicine used in adults to treat:

- a type of constipation called chronic idiopathic constipation (CIC). Idiopathic means the cause of the constipation is unknown.
- irritable bowel syndrome with constipation (IBS-C).

It is not known if TRULANCE is safe and effective in children less than 18 years of age.

Who should not take TRULANCE?

- Do not give TRULANCE to children who are less than 6 years of age.
- Do not take TRULANCE if a doctor has told you that you have a bowel blockage (intestinal obstruction).

Before taking TRULANCE, tell your doctor about all of your medical conditions, including if you:

- are pregnant or plan to become pregnant. It is not known if TRULANCE will harm your unborn baby.
- are breastfeeding or plan to breastfeed. Talk with your doctor about the best way to feed your baby if you take TRULANCE.

Tell your doctor about all the medicines you take,including prescription and over-the-counter medicines, vitamins, and herbal supplements.

How should I take TRULANCE?

- Take TRULANCE exactly as your doctor tells you to take it.
- Take TRULANCE by mouth, 1 time each day with or without food.
- If you miss a dose, skip the missed dose. Take the next dose at your regular time. Do not take 2 doses at the same time.
- TRULANCE tablets should be swallowed whole.

Adults who cannot swallow TRULANCE tablets whole may crush the TRULANCE tablet and mix with applesauce or dissolve TRULANCE in water before swallowing. TRULANCE tablets may also be taken with water by adults through a nasogastric or gastric feeding tube.

- It is not known if TRULANCE is safe and effective when crushed and mixed with other foods or dissolved in other liquids.
- Taking TRULANCE in applesauce:

- Crush the TRULANCE tablet in a clean container until it is a powder and mix with 1 teaspoon of room temperature applesauce.
- Swallow all of the TRULANCE and applesauce mixture right away. Do not keep the TRULANCE and applesauce mixture for future use.

Taking TRULANCE in water:

- Place the TRULANCE tablet in a clean cup and pour 1 ounce (30 mL) of room temperature water into the cup.
- Gently swirl the TRULANCE tablet and water for at least 10 seconds. The TRULANCE tablet will fall apart in the water.
- Swallow all of the TRULANCE tablet and water mixture right away. Do not keep the mixture for future use.
- If you see any part of the tablet left in the cup, add another 1 ounce (30 mL) of water to the cup, swirl for at least 10 seconds, and swallow right away.

Taking TRULANCE through a nasogastric or gastric feeding tube:
Gather the supplies you will need to take your TRULANCE dose. Your doctor should tell you what size catheter tip syringe you will need for your dose. Ask your doctor if you have any questions about how to give TRULANCE the right way.

- Place the TRULANCE tablet in a clean cup with 1 ounce (30 mL) of room temperature water.
- Gently swirl the TRULANCE tablet and water for at least 15 seconds. The TRULANCE tablet will fall apart in the water.
- Flush the nasogastric or gastric feeding tube with 1 ounce (30 mL) of water.
- Draw up the TRULANCE tablet and water mixture into a catheter tip syringe and give right away through the nasogastric or gastric feeding tube. Do not keep the mixture for future use.
- If you see any part of the tablet left in the cup, add another 1 ounce (30 mL) of water to the cup, swirl for at least 15 seconds and use the same catheter tip syringe to give the mixture through the nasogastric or gastric feeding tube.
- Using the same or another catheter tip syringe, flush the nasogastric or gastric feeding tube with at least 10 mL of water.

What are the possible side effects of TRULANCE?

TRULANCE can cause serious side effects, including:

- See “What is the most important information I should know about TRULANCE?”
- Diarrhea is the most common side effect of TRULANCE, and it can sometimes be severe.
- Diarrhea often begins within the first 4 weeks of TRULANCE treatment.

Stop taking TRULANCE and call your doctor if you develop severe diarrhea.
These are not all the possible side effects of TRULANCE.

Call your doctor for medical advice about side effects. You may report side effects to FDA at 1-800-FDA-1088.

How should I store TRULANCE?

- Store TRULANCE at room temperature between 68°F to 77°F (20°C to 25°C).
- Keep TRULANCE in a secure place and in the bottle that it comes in.
- The TRULANCE bottle contains a desiccant packet to help keep your medicine dry (protect it from moisture). Do not remove the desiccant packet from the bottle.
- The TRULANCE bottle contains a polyester coil to help protect the tablets during shipping. Remove the polyester coil from the bottle and throw it away after opening the bottle.
- Keep the container of TRULANCE tightly closed and in a dry place.
- Safely throw away TRULANCE that is out of date or no longer needed.

Keep TRULANCE and all medicines out of the reach of children.

- General information about the safe and effective use of TRULANCE.
  Medicines are sometimes prescribed for purposes other than those listed in a Medication Guide. Do not use TRULANCE for a condition for which it was not prescribed. Do not give TRULANCE to other people, even if they have the same symptoms that you have. It may harm them.
  You can ask your doctor or pharmacist for information about TRULANCE that is written for health professionals.

What are the ingredients in TRULANCE?
Active ingredient:plecanatide
Inactive ingredients:magnesium stearate and microcrystalline cellulose

Distributed by:
Salix Pharmaceuticals, a division of
Bausch Health US, LLC
Bridgewater, NJ 08807 USA

Patented. See https://patents.salix.comfor US patent information.

TRULANCE is a trademark of Salix Pharmaceuticals, Inc. or its affiliates.

©2024 Salix Pharmaceuticals, Inc. or its affiliates

This Medication Guide is approved by the U.S. Food and Drug Administration.

Revised: 03/2024
9705704

PRINCIPAL DISPLAY PANEL - 3 mg Tablet Label

NDC65649-003-30

Rx only
30 Tablets

Trulance®
(plecanatide) tablets

3 mg

ATTENTION PHARMACIST:
Dispense the accompanying
Medication Guide to each patient.

Keep Trulance®in the original container
to protect from moisture. Do not remove
the desiccant from inside the bottle.

9705600